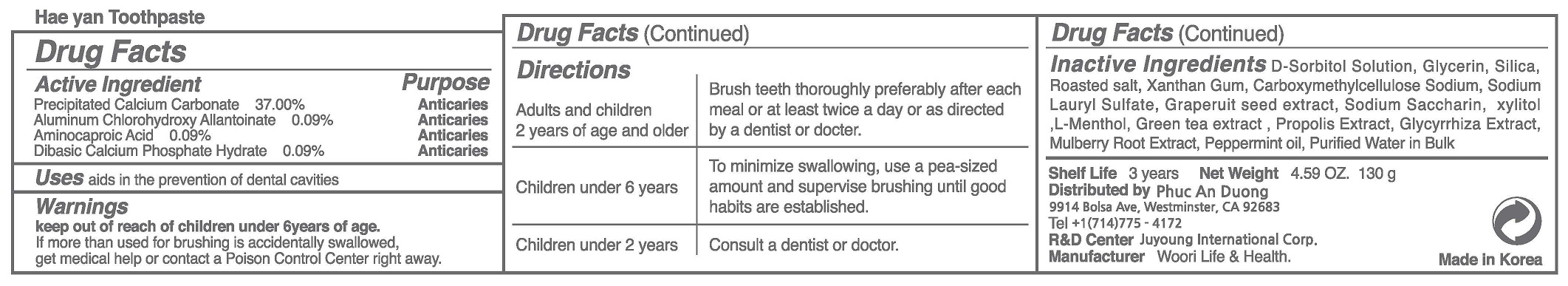 DRUG LABEL: Hea YanToothpaste
NDC: 73065-0008 | Form: PASTE, DENTIFRICE
Manufacturer: WOORI LIFE & HEALTH
Category: otc | Type: HUMAN OTC DRUG LABEL
Date: 20230423

ACTIVE INGREDIENTS: AMINOCAPROIC ACID 0.09 g/100 g; CALCIUM CARBONATE 37 g/100 g; DIBASIC CALCIUM PHOSPHATE DIHYDRATE 0.09 g/100 g; ALCLOXA 0.09 g/100 g
INACTIVE INGREDIENTS: XYLITOL; WATER

ACTIVE INGREDIENT

Precipitated Calcium Carbonate
Aluminum Chlorohydroxy Allantoinate
Aminocaproic Acid
Dibasic Calcium Phosphate Hydrate

PURPOSE

To be white and strong, Maintain and clean the mouth, Refresh the oral cavity, Prevention of tooth decay, eliminates bad breat, Enhances the aesthetic effect, Periodontitis (pyorrhea) the prevention, gum disease prevention, Prevention of gingivitis, periodontal disease prevention, gingiva diseage prevention, plaque removal (anti-plaque).

Keep out of reach of children

INDICATIONS AND USAGE

apply appropriate amount of the tooth paste on the tooth brush and brush the teeth

WARNINGS

(1) Do not swallow, gargle fully after using.
(2) If the use of this paste causes gingiva or oral cavity injury, please stop using and consult a doctor or a dentist.
(3) If childern under 6 years of age use, please apply a pea-sized amount each thime. Do not swallow. Please use under the guidance of the guardian.
(4) If children under 6 years of age accidentally ingest large amounts of the paste, please consult a doctor or a dentist immediately.
(5) Keep out of reach of children under 6 years of age.

INACTIVE INGREDIENT

D-Sorbitol Solution
Glycerin
Silica
Roasted salt
Xanthan Gum
Carboxymethylcellulose Sodium
Sodium Lauryl Sulfate
Graperuit seed extract
Sodium Saccharin
xylitol
L-Menthol
Green tea extract
Propolis Extract
Glycyrrhiza Extract
Mulberry Root Extract
Peppermint oil
Purified Water in Bulk

DOSAGE AND ADMINISTRATION

For dental use only